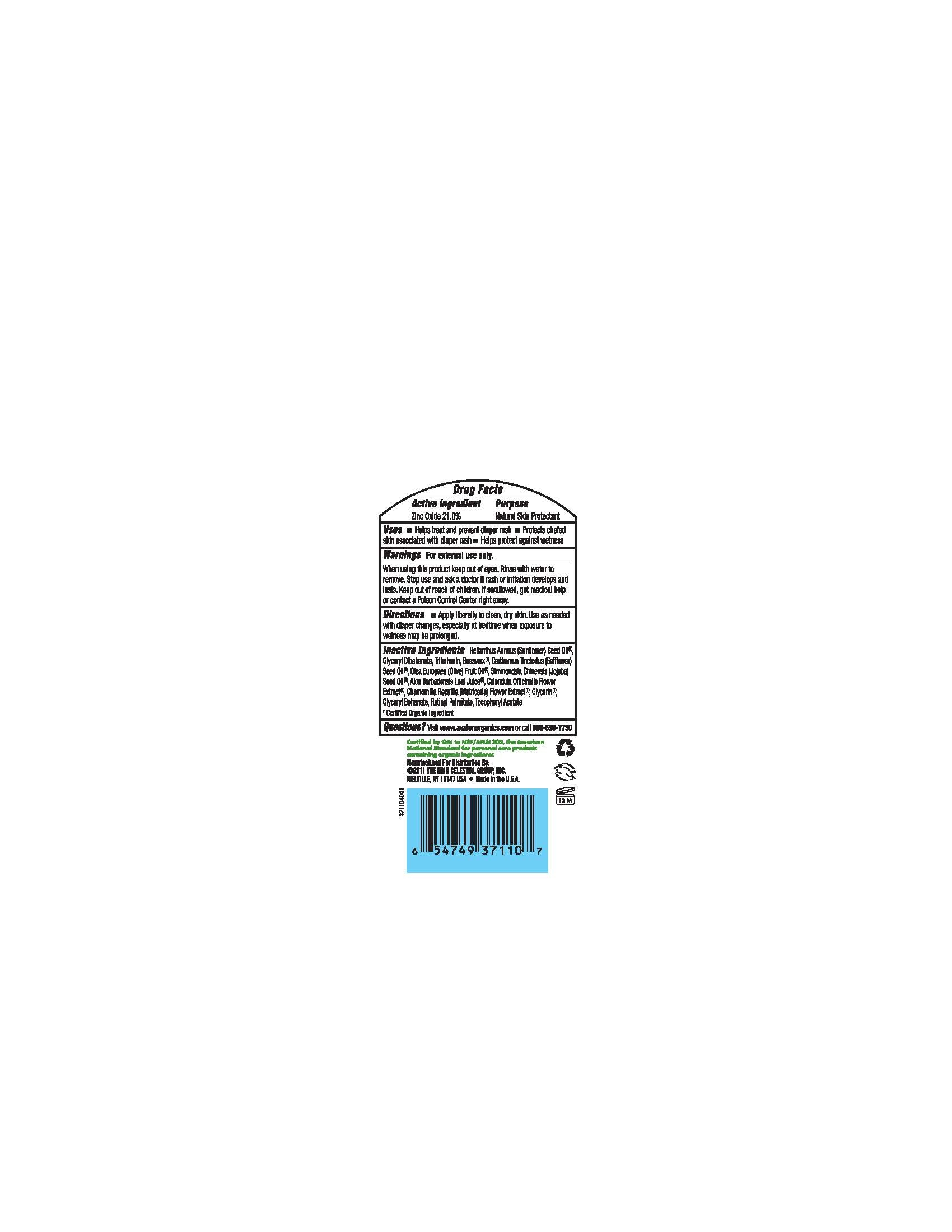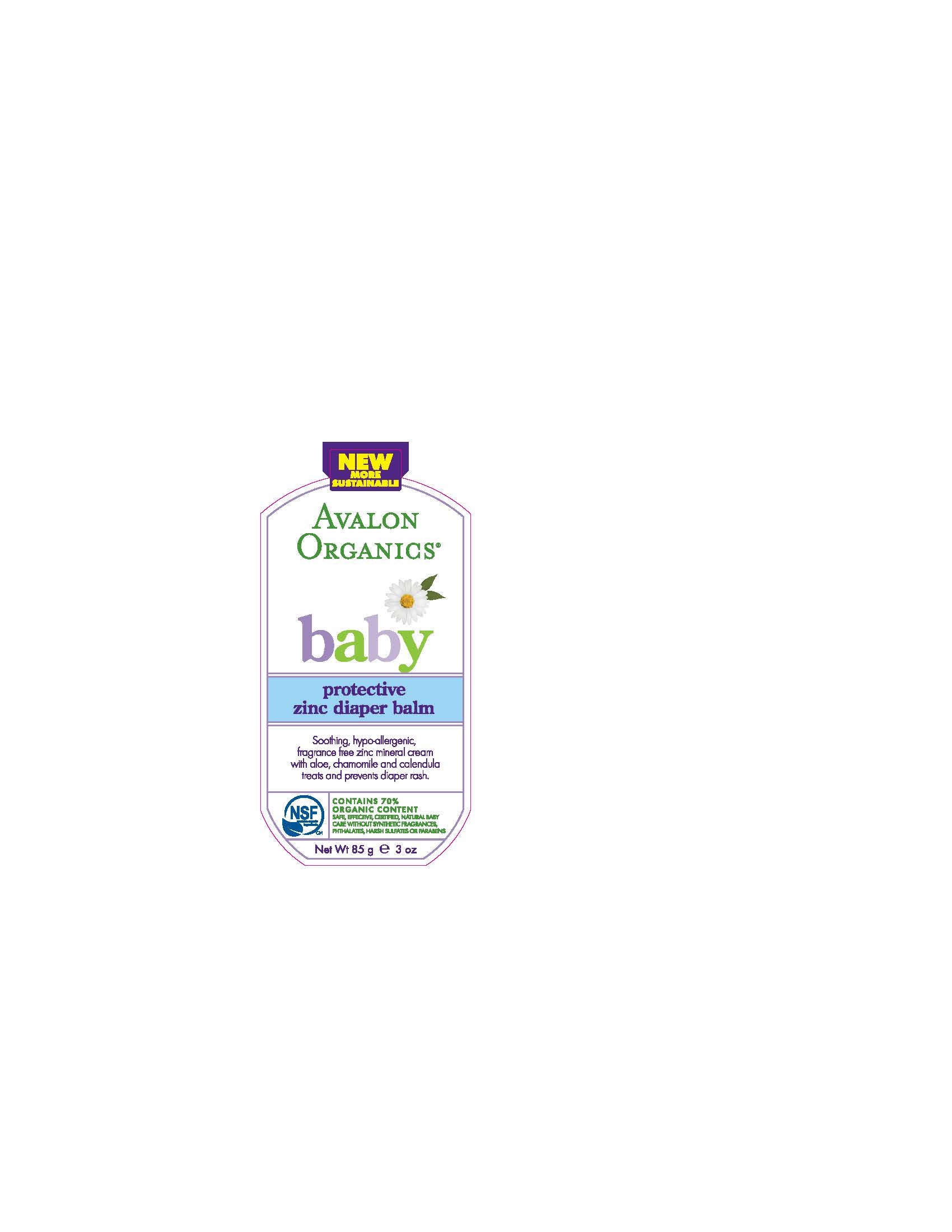 DRUG LABEL:  Avalon Organics Baby Protective Zinc Diaper Balm
NDC: 61995-1110 | Form: CREAM
Manufacturer: The Hain Celestial Group, Inc
Category: otc | Type: HUMAN OTC DRUG LABEL
Date: 20120430

ACTIVE INGREDIENTS: Zinc Oxide 21 g/100 g
INACTIVE INGREDIENTS: SUNFLOWER OIL; TRIBEHENIN; WHITE WAX

Drug Facts

ACTIVE INGREDIENT

Zinc Oxide 21.0%

PURPOSE

Natural Skin Protectant

INDICATIONS AND USAGE

- Helps treat and prevent diaper rash.
- Protects chafed skin associated with diaper rash.
- Helps protect against wetness

When using this product keep out of eyes. Rinse with water to remove. Stop use and ask doctor if rash or irritation develops and lasts.

Keep out of reach of children. If swallowed get medical help or contact Poison Center right away.

DOSAGE AND ADMINISTRATION

- Apply liberally to clean,dry skin. Use as needed with diaper changes, especially at bedtime when exposure to wetness may be prolonged.

INACTIVE INGREDIENT

Helianthus Annuus (Sunflower) Seed Oil *, Glyceryl Dibehenate, Tribehenin, Beeswax*, Carthamus Tinctorius (Safflower) Oil* , Olea Europea (Olive) Fruit Oil *, Simmondsia Chinensis (Jojoba) Seed Oil*, Aloe Barbadensis Leaf Juice* , Calendula Officinalis Flower Extract* , Chamomilla Recutita (Matricaria) Flower Extract *, Glycerin *, Glyceryl Behenate, Retinyl Palmitate, Tocopheryl Acetate.

* Certified Organic Ingredients

QUESTIONS

Questions? Visit www.avalonorganics.com or call 888-659-7730